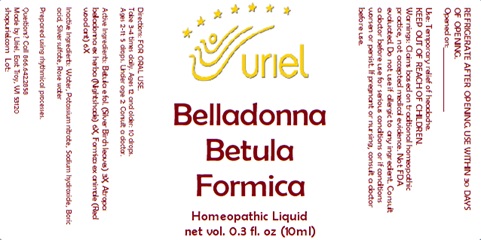 DRUG LABEL: Belladonna Betula Formica
NDC: 48951-2133 | Form: LIQUID
Manufacturer: Uriel Pharmacy Inc.
Category: homeopathic | Type: HUMAN OTC DRUG LABEL
Date: 20241204

ACTIVE INGREDIENTS: BETULA PENDULA LEAF 3 [hp_X]/1 mL; ATROPA BELLADONNA 6 [hp_X]/1 mL; FORMICA RUFA 6 [hp_X]/1 mL
INACTIVE INGREDIENTS: SILVER SULFATE; ROSMARINUS OFFICINALIS (ROSEMARY) LEAF OIL; WATER; SODIUM HYDROXIDE; BORIC ACID; POTASSIUM NITRATE

Belladonna Betula Formica

INDICATIONS AND USAGE

Directions: FOR ORAL USE.

DOSAGE AND ADMINISTRATION

Take 3-4 times daily. Ages 12 and older: 10 drops.
Ages 2-11: 5 drops. Under age 2: Consult a doctor.

ACTIVE INGREDIENT

Active Ingredients: Betula e fol. (Silver Birch leaves) 3X, Atropa belladonna ex herba (Nightshade) 6X, Formica ex animale (Red wood ant) 6X

INACTIVE INGREDIENT

Inactive Ingredients: Water, Potassium nitrate, Sodium hydroxide, Boric acid, Silver sulfate, Rose water

Prepared using rhythmical processes.

PURPOSE

Use: Temporary relief of headache.

KEEP OUT OF REACH OF CHILDREN.

WARNINGS

Warnings: Claims based on traditional homeopathic practice, not accepted medical evidence. Not FDA evaluated. Do not use if allergic to any ingredient. Consult a doctor before use for serious conditions or if conditions worsen or persist. If pregnant or nursing, consult a doctor before use. Do not use if safety seal is broken or missing.

REFRIGERATE AFTER OPENING. USE WITHIN 30 DAYS OF OPENING.
Opened on:_________________

Questions? Call 866.642.2858
Made by Uriel, East Troy, WI 53120
shopuriel.com Lot: